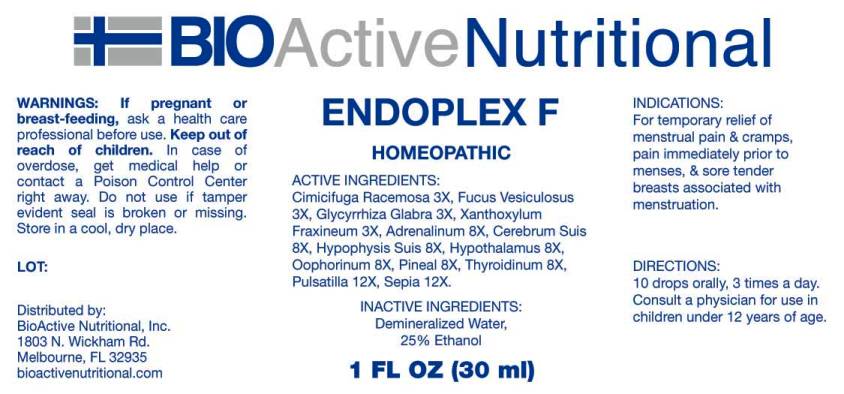 DRUG LABEL: Endoplex F
NDC: 43857-0417 | Form: LIQUID
Manufacturer: BioActive Nutritional, Inc.
Category: homeopathic | Type: HUMAN OTC DRUG LABEL
Date: 20160929

ACTIVE INGREDIENTS: BLACK COHOSH 3 [hp_X]/1 mL; FUCUS VESICULOSUS 3 [hp_X]/1 mL; GLYCYRRHIZA GLABRA 3 [hp_X]/1 mL; ZANTHOXYLUM AMERICANUM BARK 3 [hp_X]/1 mL; EPINEPHRINE 8 [hp_X]/1 mL; SUS SCROFA CEREBRUM 8 [hp_X]/1 mL; SUS SCROFA PITUITARY GLAND 8 [hp_X]/1 mL; SUS SCROFA HYPOTHALAMUS 8 [hp_X]/1 mL; SUS SCROFA OVARY 8 [hp_X]/1 mL; SUS SCROFA PINEAL GLAND 8 [hp_X]/1 mL; SUS SCROFA THYROID 8 [hp_X]/1 mL; PULSATILLA VULGARIS 12 [hp_X]/1 mL; SEPIA OFFICINALIS JUICE 12 [hp_X]/1 mL
INACTIVE INGREDIENTS: WATER; ALCOHOL

Drug Facts:

ACTIVE INGREDIENTS:

Cimicifuga Racemosa 3X, Fucus Vesiculosus 3X, Glycyrrhiza Glabra 3X, Xanthoxylum Fraxineum 3X, Adrenalinum 8X, Cerebrum Suis 8X, Hypophysis Suis 8X, Hypothalamus (Suis) 8X, Oophorinum (Suis) 8X, Pineal (Suis) 8X, Thyroidinum (Suis) 8X, Pulsatilla (Vulgaris) 12X, Sepia 12X.

INDICATIONS:

For temporary relief of menstrual pain and cramps, pain immediately prior to menses, and sore tender breasts associated with menstruation.

WARNINGS:

If pregnant or breast-feeding, ask a health care professional before use.

Keep out of reach of children. In case of overdose, get medical help or contact a Poison Control Center right away.

Do not use if tamper evident seal is broken or missing.

Store in cool, dry place.

Keep out of reach of children. In case of overdose, get medical help or contact a Poison Control Center right away.

DIRECTIONS:

10 drops orally, 3 times a day. Consult a physician for use in children under 12 years of age.

INDICATIONS:

For temporary relief of menstrual pain and cramps, pain immediately prior to menses, and sore tender breasts associated with menstruation.

INACTIVE INGREDIENTS:

Demineralized Water, 25% Ethanol

QUESTIONS:

Distributed by:
BioActive Nutritional, Inc.
1803 N. Wickham Rd.
Melbourne, FL 32935
bioactivenutritional.com

PACKAGE LABEL DISPLAY:

BIOActive Nutritional

ENDOPLEX F

HOMEOPATHIC

1 FL OZ (30 ml)